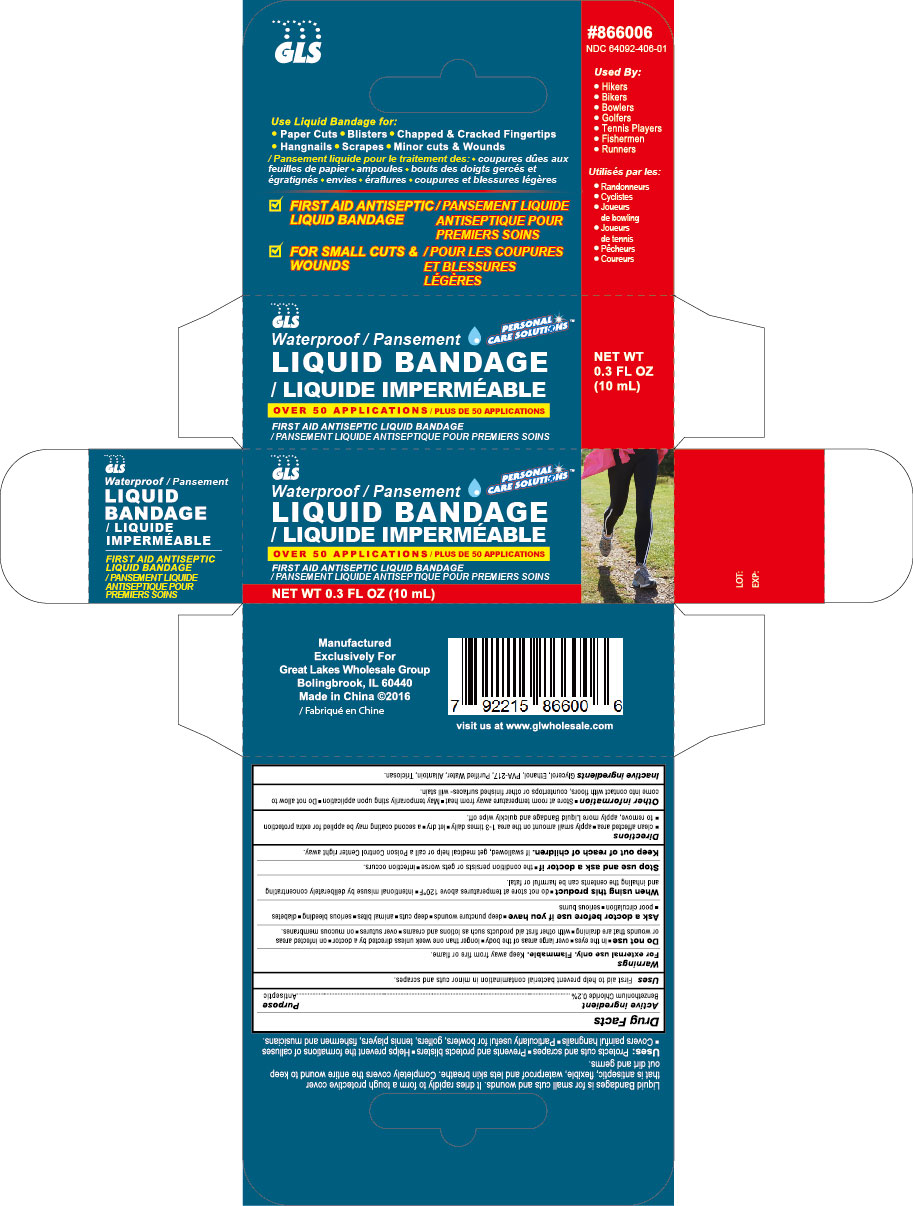 DRUG LABEL: Liquid Bandage
NDC: 64092-406 | Form: LIQUID
Manufacturer: Great Lakes Wholesale, Marketing, and Sales, Inc
Category: otc | Type: HUMAN OTC DRUG LABEL
Date: 20161205

ACTIVE INGREDIENTS: BENZETHONIUM CHLORIDE 0.02 g/10 mL
INACTIVE INGREDIENTS: GLYCEROL 1,3-DIMETHACRYLATE

ACTIVE INGREDIENT

Benzethonuim Chloride 0.2%

PURPOSE

Antiseptic for small cuts and wounds.

INDICATIONS AND USAGE

- Protects cuts and scrapes
- Prevents and protects blisters
- Helps prevent the formations of calluses
- Covers painful hangnails
- Particularly useful for bowlers, golfers, tennis players, fishermen and musicians.

It dries rapidly to form a tough protective cover that is antiseptic, flexible, waterproof and lets skin breathe.

First aid to help prevent bacterial contamination in minor cuts and scrapes.

WARNINGS

For external ue only. Flammable. Keep away from fire or flame.

Do not use

- in the eyes
- over large areas of the body
- longer than one week unless directed by a doctor
- on infected areas or wounds that are draining
- with other first aid products, such as lotions and creams
- over sutures
- on mucous membranes

Ask a doctor before use if you have

- deep puncture wounds
- deep cuts
- animal bites
- serious bleeding
- diabetes
- poor circulation
- serious burns

Stop use and ask a doctor if

- the condition persists or gets worse
- infection occurs

KEEP OUT OF REACH OF CHILDREN

If swallowed, get medical help or call a Poison Control Center right away.

When using this product

- do not store at temperatures above 120º F
- intentional misuse by deliberately concentrating and inhaling the centents can be harmful or fatal

Other information

- Store at room temperature away from heat
- May temporarily sting upon application
- Do not allow to come into contact with floors, countertops or other finished surfaces - will stain

Directions

- clean affected area
- apply small amount on the area 1-3 times daily
- let dry
- a second coating may be applied for extra protection
- to remove, apply more Liquid Bandage and quickly wipe off.

INACTIVE INGREDIENT

Glycerol, Ethanol, PVA-217, Purified Water, Allantion, Triclosan.

DOSAGE AND ADMINISTRATION

- Clean affected area
- apply a small amount on the area 1-3 times daily
- let dry
- a second coating may be applied for extra protection.

DESCRIPTION

GLS

Personal Care Solutions

Waterproof Liquid Bandage

First Aid Antiseptic Liquid Bandage

For small cuts & wounds

Over 50 applications

First Aid Antiseptic Liquid Bandage

0.3 Fl oz. (10 mL)

Used By:

- Hikers
- Bikers
- Bowlers
- Golfers
- Tennis Players
- Fishermen
- Runners

Liquid Bandages is for small cuts and wounds. It dries rapidly to form a tough protective cover that is antiseptic, flexible, waterproof and lets skin breathe. Completely covers the entire wound to keep out dirt and germs. Try it spray for larger areas.